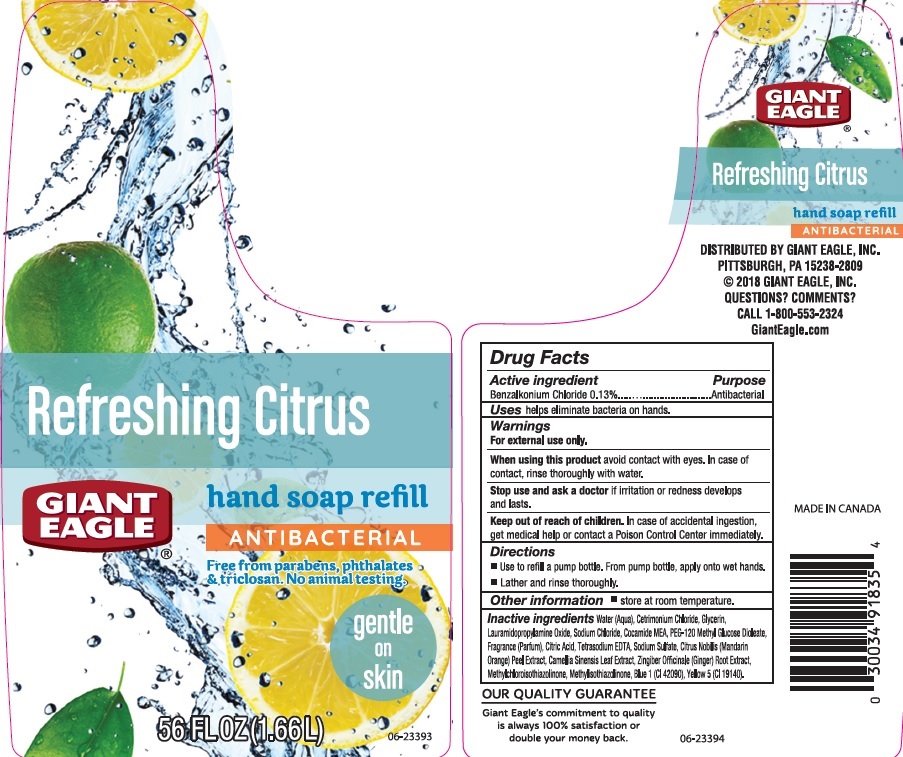 DRUG LABEL: Giant Eagle Refreshing Citrus
NDC: 63148-724 | Form: LIQUID
Manufacturer: Apollo Health and Beauty Care Inc.
Category: otc | Type: HUMAN OTC DRUG LABEL
Date: 20180913

ACTIVE INGREDIENTS: BENZALKONIUM CHLORIDE 1.3 mg/1 mL
INACTIVE INGREDIENTS: WATER; CETRIMONIUM CHLORIDE; GLYCERIN; LAURAMIDOPROPYLAMINE OXIDE; SODIUM CHLORIDE; COCO MONOETHANOLAMIDE; PEG-120 METHYL GLUCOSE DIOLEATE; CITRIC ACID MONOHYDRATE; EDETATE SODIUM; SODIUM SULFATE; CITRUS NOBILIS; GREEN TEA LEAF; GINGER; METHYLCHLOROISOTHIAZOLINONE; METHYLISOTHIAZOLINONE; FD&C BLUE NO. 1; FD&C YELLOW NO. 5

Drug Facts

Active ingredient

Benzalkonium Chloride 0.13%

Purpose

Antibacterial

Uses

helps eliminate bacteria on hands.

Warnings

For external use only

When using this product

avoid contact with eyes. In case of contact, rinse thoroughly with water.

Stop use and ask a doctor if

irritation or redness develops and lasts.

Keep out of reach of children.

In case of accidental ingestion, get medical help or contact a Poison Control Center immediately.

Directions

- Use to refill a pump bottle. From pump bottle, apply onto wet hands.
- Lather and rinse thoroughly.

Other information

- store at room temperature

Inactive ingredients

Water (Aqua), Cetrimonium Chloride, Glycerin, Lauramidopropylamine Oxide, Sodium Chloride, Cocamide MEA, PEG-120 Methyl Glucose Dioleate, Fragrance (Parfum), Citric Acid, Tetrasodium EDTA, Sodium Sulfate, Citrus Nobilis (Mandarin Orange) Peel Extract, Camelilla Sinensis Leaf Extract, Zingiber Officinale (Ginger) Root Extract, Methylchloroisothiazolinone, Methylisothiazolinone, Blue 1 (CI 42090), Yellow 5 (CI 19140).